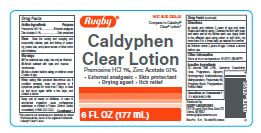 DRUG LABEL: Rugby Caldyphen Clear
NDC: 0536-1269 | Form: LOTION
Manufacturer: Rugby Laboratories
Category: otc | Type: HUMAN OTC DRUG LABEL
Date: 20250728

ACTIVE INGREDIENTS: PRAMOXINE HYDROCHLORIDE 10 mg/1 mL; ZINC ACETATE 1 mg/1 mL
INACTIVE INGREDIENTS: METHYLPARABEN; POLYSORBATE 80; PROPYLENE GLYCOL; PROPYLPARABEN; WATER; CAMPHOR (NATURAL); ALCOHOL; DIAZOLIDINYL UREA; GLYCERIN; HYPROMELLOSE, UNSPECIFIED

Rugby Caldyphen Clear Lotion

ACTIVE INGREDIENT

Pramoxine HCl 1%

Zing Acetate 0.1%

PURPOSE

External Analgesic

Skin Protectant

INDICATIONS AND USAGE

Dries the oozing and weeping and temporarily relieves pain and itching of poison ivy, poison oak, and poison sumac or other minor skin irritations.

WARNINGS

For external use only. Use only as directed.

Avoid contact with eyes and mucous membranes.

Ask a doctor before using

on children under 2 years of age.

When using this product. Discontinue use if

condition worsens, does not improve or if symptoms persist for more than 7 days, or clear up and occur again within a few days. and consult a doctor.

Keep out of reach of children.

In case of accidental ingestion, seek professional assistance or contact a Poison Control Center immediately.

DOSAGE AND ADMINISTRATION

Adults and children 2 yrs. of age and older. Shake well before using. Cleanse the skin with soap and water and let dry before each use. Apply lotion to the affected area using cotton or soft cloth, not more than 3 to 4 times daily as needed for comfort.
Children under 2 years of age: Consult a doctor before use.

INACTIVE INGREDIENT

SD Alcohol 38B 2.5%, Camphor, Diazolidinyl Urea, Fragrances, Glycerin, Hydroxypropyl Methylcellulose, Methylparaben, Polysorbate 80, Propylene Glycol, Propylparaben, Purified Water.

KEEP OUT OF REACH OF CHILDREN

In case of accidental ingestion, seek professional assistance or contact a poison control center immediately.